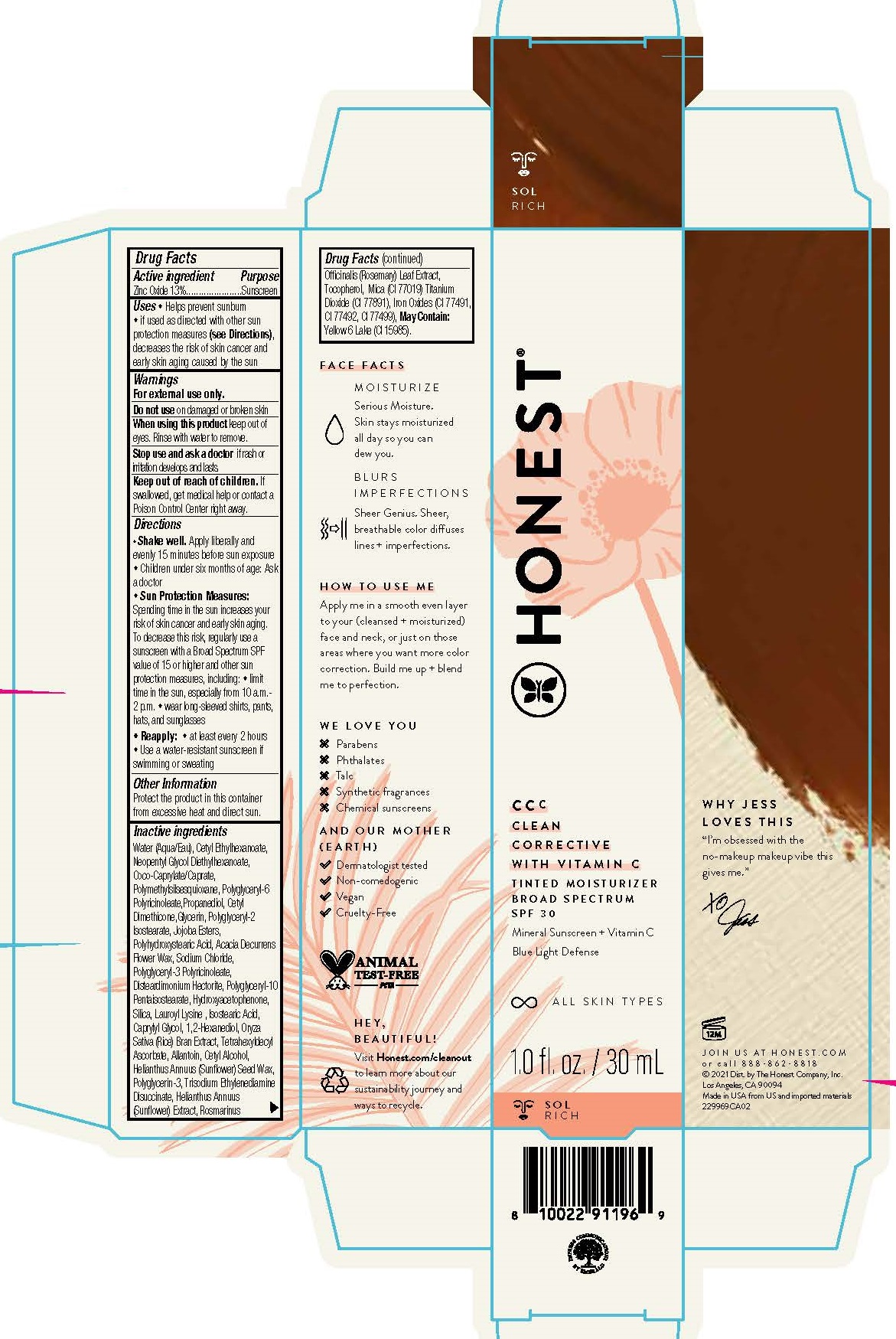 DRUG LABEL: CCC Clean Corrective with Vitamin C Tinted Moisturizer Broad Spectrum SPF 30
NDC: 69366-223 | Form: LOTION
Manufacturer: The Honest Company, Inc.
Category: otc | Type: HUMAN OTC DRUG LABEL
Date: 20231205

ACTIVE INGREDIENTS: ZINC OXIDE 13 mg/100 mL
INACTIVE INGREDIENTS: TRISODIUM ETHYLENEDIAMINE DISUCCINATE; FERROSOFERRIC OXIDE; MICA; POLYGLYCERYL-10 PENTASTEARATE; CETYL DIMETHICONE 150; SODIUM CHLORIDE; POLYGLYCERYL-3 RICINOLEATE; TOCOPHEROL; POLYGLYCERYL-2 ISOSTEARATE; SILICON DIOXIDE; LAUROYL LYSINE; ISOSTEARIC ACID; 1,2-HEXANEDIOL; WATER; CETYL ETHYLHEXANOATE; POLYHYDROXYSTEARIC ACID (2300 MW); FD&C YELLOW NO. 6; ROSEMARY; TITANIUM DIOXIDE; NEOPENTYL GLYCOL DIETHYLHEXANOATE; POLYGLYCERYL-6 POLYRICINOLEATE; GLYCERIN; ACACIA DECURRENS FLOWER WAX; DISTEARDIMONIUM HECTORITE; HYDROGENATED JOJOBA OIL/JOJOBA OIL, RANDOMIZED (IODINE VALUE 40-44); HELIANTHUS ANNUUS FLOWERING TOP; FERRIC OXIDE RED; FERRIC OXIDE YELLOW; COCO-CAPRYLATE/CAPRATE; POLYMETHYLSILSESQUIOXANE (4.5 MICRONS); PROPANEDIOL; 3'-HYDROXYACETOPHENONE; CAPRYLYL GLYCOL; RICE BRAN; TETRAHEXYLDECYL ASCORBATE; ALLANTOIN; CETYL ALCOHOL; HELIANTHUS ANNUUS SEED WAX; POLYGLYCERIN-3

Tinted Moisturizer SPF 30 Sol

Active ingredient Zinc Oxide 13%

Purpose Sunscreen

INDICATIONS AND USAGE

Uses Helps prevent sunburn if used as directed with other sun protection measures (see Directions), decreases the risk of skin cancer and early skin aging caused by the sun

Warnings

For external use only.

Do not use on damaged or broken skin

When using this product keep out of eyes. Rinse with water to remove.

Stop use and ask a doctor if rash or irritation develops and lasts

Keep out of reach of children. If swallowed, get medical help or contact a Poison Control Center right away.

Directions

- Shake well. Apply liberally and evenly 15 minutes before sun exposure
- Children under six months of age: ask a doctor
- Sun Protection Measures: Spending time in the sun increases your risk of skin cancer and early skin aging. To decrease this risk, regularly use a sunscreen with a Broad Spectrum SPF vaue of 15 or higher and other sun protection measures, including: ♦ limit time in the sun, especially from 10 a.m.-2 p.m. ♦ wear long sleeved shirts, pants, hats, and sunglasses
- Reapply: at least every 2 hours
- Use a water-resistant sunscreen if swimming or sweating

Other information Protect the product in this container from excessive heat and direct sun.

INACTIVE INGREDIENT

Inactive ingredients Water (Aqua/Eau), Cetyl Ethylhexanoate, Neopentyl Glycol Diethylhexanoate, Coco-Caprylate/Caprate, Polymethylsilsesquioxane, Polyglyceryl-6 Polyricinoleate, Propanediol, Cetyl Dimethicone, Glycerin, Polyglyceryl-2 Isostearate, Jojoba Esters, Polyhydroxystearic Acid, Acacia Decurrens Flower Wax, Sodium Chloride, Polyglyceryl-3 Polyricinoleate, Disteardimonium Hectorite, Polyglyceryl-10 Pentaisostearate, Hydroxyacetophenone, Silica, Lauroyl Lysine, Isostearic Acid, Caprylyl Glycol, 1,2-Hexanediol, Oryza Sativa (Rice) Bran Extract, Tetrahexyldecyl Ascorbate, Allantoin, Cetyl Alcohol, Helianthus Annuus (Sunflower) Seed Wax, Polyglycerin-3, Trisodium Ethylenediamine Disuccinate, Helianthus Annuus (Sunflower) Extract, Rosmarinus Officinalis (Rosemary) Leaf Extract, Tocopherol, Mica (CI 77019), Titanium Dioxide (CI 77891), Iron Oxides (CI 77491), Iron Oxides (CI 77492), Iron Oxides (CI 77499) May Contain, Yellow 6 Lake (CI 15985)

HONEST®

CCc

CLEAN CORRECTIVE WITH VITAMIN C

Tinted Moisturizer

Broad Spectrum SPF 30

Mineral Sunscreen + Vitamin C

Blue Light Defense

1.0 fl. oz./ 30 mL

Joins us at HONEST.COM or call 888-862-8818

©2021 Dist. by The Honest Company, Inc.

Los Angeles, CA 90094

Made in USA from US and imported materials